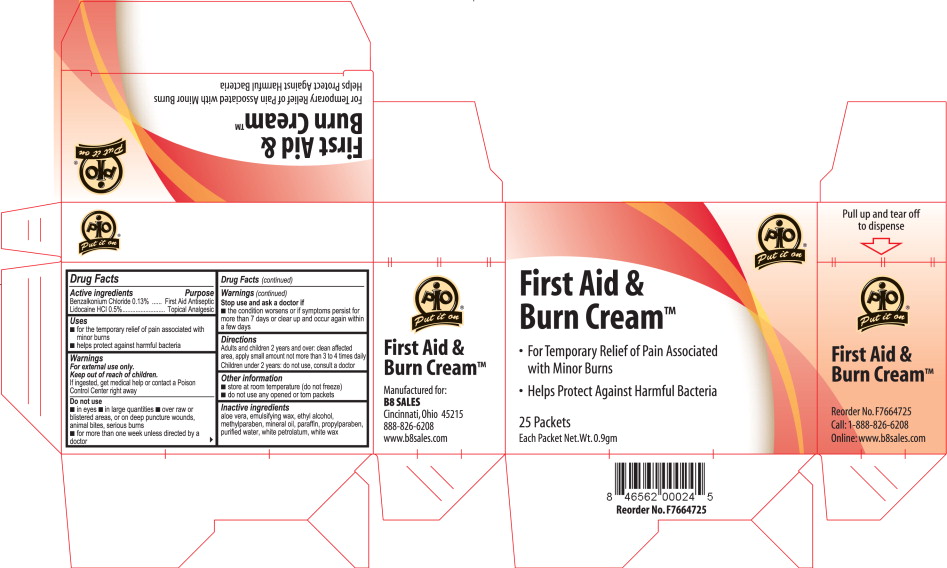 DRUG LABEL: First aid and Burn
NDC: 50607-5700 | Form: CREAM
Manufacturer: B8 Sales, Inc.
Category: otc | Type: HUMAN OTC DRUG LABEL
Date: 20100402

ACTIVE INGREDIENTS: Benzalkonium Chloride 1.3 mg/1 g; Lidocaine Hydrochloride 5 mg/1 g
INACTIVE INGREDIENTS: aloe; alcohol; methylparaben; mineral oil; paraffin; propylparaben; water; petrolatum; white wax

PIO Put it on®

First Aid & Burn CreamTM

- For Temporary Relief of Pain Associated with Minor Burns
- Helps Protect Against Harmful Bacteria

25 Packets

Each Packet Net.Wt.0.9gm

Active ingredients

Benzalkonium Chloride 0.13%

Lidocaine HCI 0.5%

Purpose

First Aid Antiseptic

Topical Analgesic

Uses

- for the temporary relief of pain associated with minor bums
- helps protect against harmful bacteria

Warnings

For external use only.

Keep out of reach of children.

If ingested, get medical help or contact a Poison Control Center right away

Do not use

- in eyes ■ in large quantities ■ over raw or blistered areas, or on deep puncture wounds, animal bites, serious burns
- for more than one week unless directed by a doctor

Stop use and ask a doctor if

- the condition worsens or if symptoms persist for more than 7 days or clear up and occur again within a few days

Directions

Adults and children 2 years and over: clean affected area, apply small amount not more than 3 to 4 times daily Children under 2 years: do not use, consult a doctor

Other information

- store at room temperature (do not freeze)
- do not use any opened or torn packets

Inactive ingredients

aloe vera, emulsifying wax, ethyl alcohol, methylparaben, mineral oil, paraffin, propylparaben, purified water, white petrolatum, white wax

Principal Display Panel

First Aid & Burn Cream – Carton Label

PIO Put it on®

First Aid & Burn CreamTM

- For Temporary Relief of Pain Associated with Minor Burns
- Helps Protect Against Harmful Bacteria

25 Packets

Each Packet Net.Wt.0.9gm